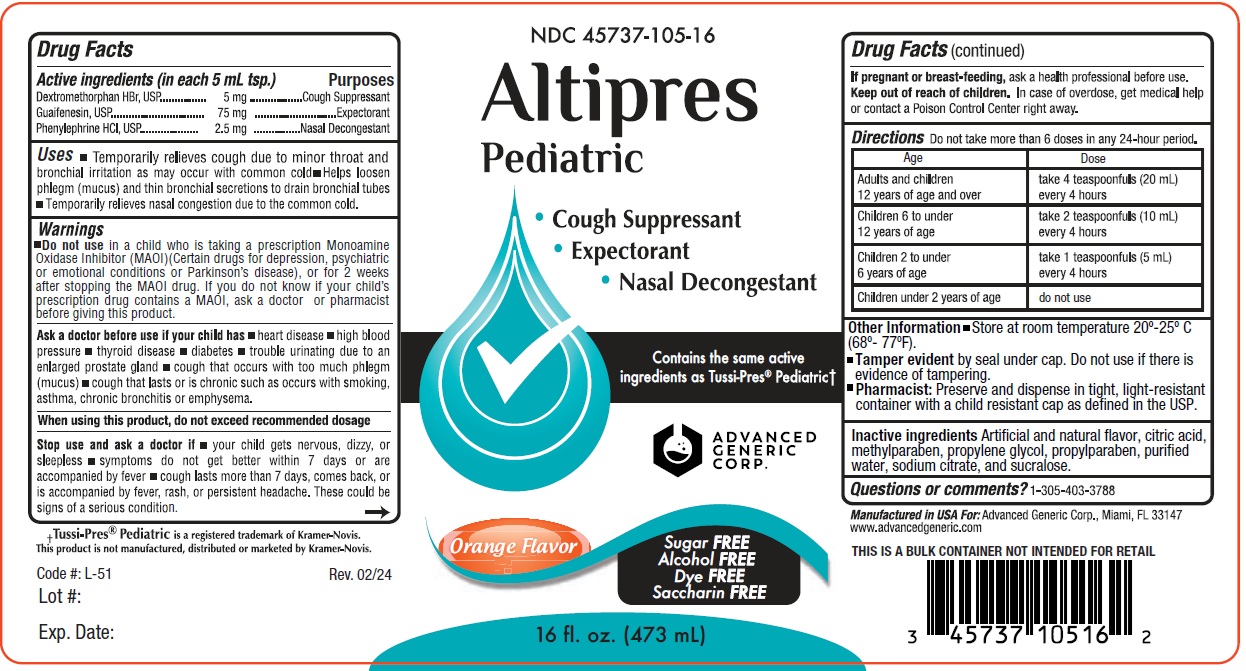 DRUG LABEL: Altipres Pediatric
NDC: 45737-105 | Form: LIQUID
Manufacturer: Advanced Generic Corporation
Category: otc | Type: HUMAN OTC DRUG LABEL
Date: 20251230

ACTIVE INGREDIENTS: DEXTROMETHORPHAN HYDROBROMIDE 5 mg/5 mL; GUAIFENESIN 75 mg/5 mL; PHENYLEPHRINE HYDROCHLORIDE 2.5 mg/5 mL
INACTIVE INGREDIENTS: SUCRALOSE; CITRIC ACID MONOHYDRATE; METHYLPARABEN; GLYCERIN; PROPYLPARABEN; WATER; SODIUM CITRATE; PROPYLENE GLYCOL

Alt-AltipresPed 105

Active Ingredients (in each 5 mL tsp.) Purpose

Dextromethorphan HBr ............... 5 mg ................ Cough Suppressant

Guaifenesin .............................. 75 mg ................ Expectorant

Phenylephrine HCl ..................... 2.5 mg ................... Nasal Decongestant

Purpose

Cough Suppressant

Expectorant

Nasal Decongestant

Uses

- temporarily relieves cough due to minor throat and bronchial irritations as may occur with the common cold
- helps loosen phlegm (mucus) and thin bronchial secretions to drain bronchial tubes
- temporarily releives nasal congestion due to the common cold.

Warnings

Do not use in a child who is taking a prescription Monoamine Oxidase Inhibitor (MAOI) (certain drugs for depression, psychiatric or emotional conditions or Parkinson's disease), or for 2 weeks after stopping the MAOI drug. If you do not know if your child's prescription drug contains an MAOI; ask your doctor or pharmacist before taking this product.

Ask a doctor before use if your child has

- heart disease
- high blood pressure
- thyroid disease
- diabetes
- trouble urinating due to enlargement of prostate gland
- a cough that occurs with too much phlegm (mucus)
- cough that lasts or is chrinic such as occurs with smoking, asthma, chronic bronchitis or emphysema.

When using this product do not exceed recommended dosage

Stop use and ask a doctor if

- your child gets nervous, dizzy, or sleepless
- symptoms do not get better within 7 days or are accompanied by fever
- cough lasts for more than 7 days, comes back or is accompanied with a fever, rash or persistent headache. These could be signs of serious condition.

PREGNANCY OR BREAST FEEDING

If pregnant or breast-feeding,ask a health professional before use.

Keep out of reach of children.In case of accidental overdose, get medical help or contact a Poison Control Center right away.

DOSAGE AND ADMINISTRATION

Directions Do not exceed more than 6 doses in any 24-hour period.

Age | Dose
Adults and children 12 years of age and over | take 4 teaspoonfuls (20 mL) every 4 hours
Children 6 to under 12 years of age | take 2 teaspoonfuls (10 mL) every 4 hours
Children 2 to under 6 years of age | take 1 teaspoonfuls (5 mL) every 4 hours
Children under 2 years of age | do not use

INACTIVE INGREDIENT

Inactive ingredients:Artificial and natural flavors, Citric acid, methylparaben, propylene glycol, propylparaben, purified water, sodium citrate, and sucralose

Questions or comments?1-305-403-3788